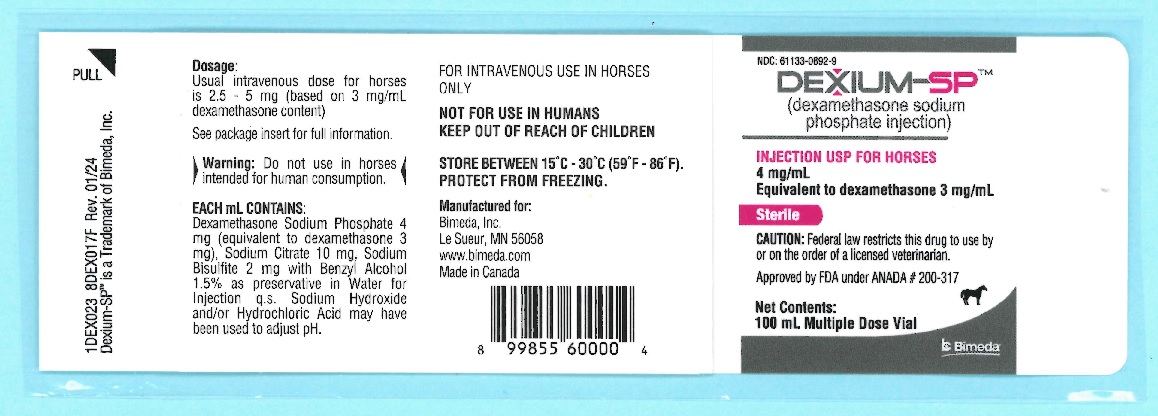 DRUG LABEL: Dexium-SP
NDC: 61133-0892 | Form: INJECTION, SOLUTION
Manufacturer: Bimeda, Inc.
Category: animal | Type: PRESCRIPTION ANIMAL DRUG LABEL
Date: 20250319

ACTIVE INGREDIENTS: DEXAMETHASONE SODIUM PHOSPHATE 3 mg/1 mL

DESCRIPTION

Dexamethasone-SPTM
(dexamethasone sodium phosphate injection)
INJECTION USP FOR HORSES
4 mg/mL
Equivalent to dexamethasone 3 mg/mL
FOR INTRAVENOUS USE IN HORSES ONLY
NOT FOR USE IN HUMANS
KEEP OUT OF REACH OF CHILDREN
WARNING: DO NOT USE IN HORSES INTENDED FOR HUMAN CONSUMPTION

CAUTION:
Federal law restricts this drug to use by or on the order of a licensed veterinarian.

DESCRIPTION:
Dexamethasone sodium phosphate (a synthetic adrenocortical steroid), is a white or slightly yellow crystalline powder. It is freely soluble in water and is exceedingly hygroscopic.

Each mL of Dexamethasone-SP (dexamethasone sodium phosphate injection) contains Dexamethasone Sodium Phosphate 4 mg (equivalent to dexamethasone 3 mg), Sodium Citrate 10 mg, Sodium Bisulfite 2 mg, Benzyl Alcohol 1.5% as a preservative, in Water for Injection q.s. Sodium Hydroxide and/or Hydrochloric Acid to adjust pH to between 7.0 and 8.5.

CLINICAL PHARMACOLOGY:
Dexamethasone is a synthetic corticosteroid and possesses glucocorticoid activity.

Dexamethasone sodium phosphate is a salt of dexamethasone that is particularly suitable for intravenous administration because it is highly water soluble, permitting administration of relatively large doses in a small volume of diluent.

Dexamethasone, as a steroid, is equivalent in potency to some established steroids while being considerably more potent than others. In the case of the dog, dexamethasone is found to be about equivalent in dosage to prednisone but about 30 to 40 times more potent than prednisolone.

INDICATIONS AND USAGE:
Dexamethasone-SP (dexamethasone sodium phosphate injection) is indicated as a rapid adrenal glucocorticoid and/or anti-inflammatory agent in horses.

CONTRAINDICATIONS:
Do not use in viral infections. Except when used for emergency therapy, dexamethasone sodium phosphate is contraindicated in animals with tuberculosis and chronic nephritis. Existence of congestive heart failure, osteoporosis and diabetes are relative contraindications.

In the presence of infection appropriate antibacterial agents should also be administered and should be continued for at least 3 days after discontinuance of the hormone and disappearance of all signs of infection.

WARNINGS:
Clinical and experimental data have demonstrated that corticosteroids administered orally or by injection to animals may induce the first stage of parturition if used during the last trimester of pregnancy and may precipitate premature parturition followed by dystocia, fetal death, retained placenta and metritis.

Additionally, corticosteroids administered to dogs, rabbits, and rodents during pregnancy have produced cleft palate. Other congenital anomalies including deformed forelegs, phocomelia, and anasarca have been reported in offspring of dogs which received corticosteroids during pregnancy.

PRECAUTIONS:
Because of the anti-inflammatory action of corticosteroids, signs of infection may be hidden and it may be necessary to stop treatment until diagnosis is made. Overdosage of some glucocorticoids may result in sodium retention, fluid retention, potassium loss and weight gains.

In infections characterized by overwhelming toxicity, dexamethasone sodium phosphate therapy, in conjunction with indicated antibacterial therapy, is effective in reducing mortality. It is essential that the causative organism be known and an effective antibacterial agent be administered concurrently. The injudicious use of adrenal hormones in animals with infections can be hazardous.

Use of corticosteroids, depending on dose, duration and specific steroid, may result in inhibition of endogenous steroid production following drug withdrawal. In patients presently receiving or recently withdrawn from systemic corticosteroid treatments, therapy with a rapidly acting corticosteroid should be considered in unusually stressful situations.

ADVERSE REACTIONS:
The therapeutic use of dexamethasone sodium phosphate injection is unlikely to cause undesired accentuation of metabolic effects. However, if continued corticosteroid therapy is anticipated, a high protein intake should be provided to keep the animal in positive nitrogen balance. A retardant effect on wound healing should be considered when it is used in conjunction with surgery. Euphoria or an improvement of attitude, and increased appetite are the usual manifestations.

Side effects such as glycosuria, hyperglycemia, diarrhea, polydipsia and polyuria have been observed in some species.

Side effects such as SAP and SGPT enzyme elevations, eosinopenia, and vomiting have occurred following use of synthetic corticosteroids in dogs.

Cushing's Syndrome in dogs has been reported in association with prolonged or repeated steroid therapy.

Corticosteroids reportedly cause laminitis in horses.

CONTACT INFORMATION:

To report suspected adverse events, for technical assistance or to obtain a copy of the Safety Data Sheet (SDS), contact Bimeda, Inc. at 1-888-524-6332. For additional information about adverse drug experience reporting for animal drugs, contact FDA at 1-888-FDA-VETS or online at https://www.fda.gov/reportanimalae.

DOSAGE AND ADMINISTRATION:
For Intravenous Use Only.
Horses: The usual intravenous dosage is 2.5 to 5 mg (based on 3 mg per mL of dexamethasone content).

If permanent corticosteroid effect is required, oral therapy with dexamethasone may be substituted. When therapy is to be withdrawn after prolonged corticosteroid administration, the daily dose should be reduced gradually over a number of days, in stepwise fashion.

HOW SUPPLIED:
Dexamethasone-SP (dexamethasone sodium phosphate injection) 4 mg/mL (equivalent to 3 mg/mL dexamethasone) is available in 100 mL multiple dose vials.

STORAGE AND HANDLING

STORE BETWEEN 15°C and 30°C (56° F and 86°F). PROTECT FROM FREEZING.

Approved by FDA under ANADA # 200-317